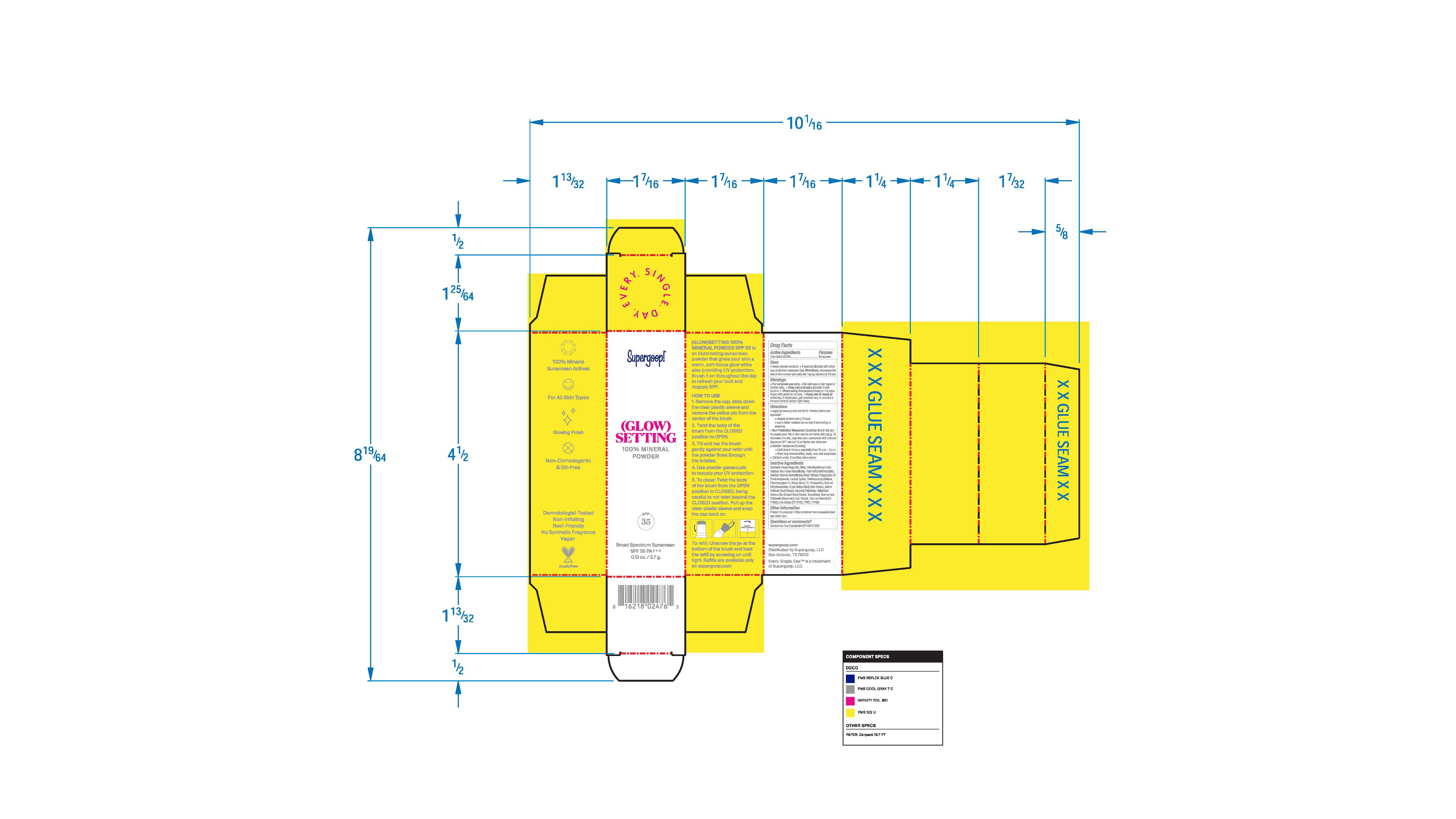 DRUG LABEL: (Glow)Setting 100% Mineral Powder SPF 35
NDC: 75936-603 | Form: POWDER
Manufacturer: Supergoop, LLC
Category: otc | Type: HUMAN OTC DRUG LABEL
Date: 20241205

ACTIVE INGREDIENTS: ZINC OXIDE 24.9 g/100 g
INACTIVE INGREDIENTS: SODIUM DEHYDROACETATE; HELIANTHUS ANNUUS SEED WAX; FERRIC OXIDE RED; FERROSOFERRIC OXIDE; MAGNESIUM POTASSIUM ALUMINOSILICATE FLUORIDE; FERRIC OXIDE YELLOW; NYLON-12; TRIMETHYLSILOXYSILICATE (M/Q 0.6-0.8); CALCIUM ALUMINUM BOROSILICATE; SILICON DIOXIDE; POLY(METHYL METHACRYLATE; 450000 MW); TRIETHOXYCAPRYLYLSILANE; BORON NITRIDE; LAUROYL LYSINE; PROPANEDIOL; FERRICLATE CALCIUM SODIUM; POLYGLYCERYL-10 PENTASTEARATE; ETHYLHEXYLGLYCERIN; ORYZA SATIVA WHOLE; ALETRIS FARINOSA ROOT; ASCORBYL PALMITATE; TOCOPHEROL; ROSMARINUS OFFICINALIS FLOWER; TITANIUM DIOXIDE; WATER

(Glow)Setting 100% Mineral Powder SPF 35

(Glow)setting 100% Mineral Powder

Zinc Oxide 2.4% Sunscreen

Uses

- Helps prevent sunburn
- If used as directed with other sun protection measures (see Directions), decreases the risk of skin cancer and early sking aging caused by the sun

- Keep out of reach of children
- If product is swallowed, get medical help or contact a Poison Control Center right away

Stop use and ask a doctor if rash occurs

Directions

• apply generously and evenly 15 minutes before sun exposure

• reapply at least every 2 hours

• use a water resistant sunscreen if swimming or sweating

• Sun Protection Measures: Spending time in the sun increases your risk of skin cancer and early skin aging. To decrease this risk, regularly use a sunscreen with a Broad Spectrum SPF value of 15 or higher and other sun protection measures including:

◦ Limit time in the sun, especially from 10 a.m. - 2 p.m.

◦ Wear long-sleeved shirts, pants, hats, and sunglasses

• Children under 6 months: Ask a doctor

Warnings

- For external use only
- Do not use on damaged or broken skin
- Stop use and ask a doctor if rash occurs
- When using this product keep out of eyes
- Rinse with water to remove

Inactive Ingredients

Synthetic Fluorphlogopite, Silica, Trimethylsiloxysilicate, Calcium Aluminum Borosilicate, Polymethyl Methacrylate, Calcium Sodium Borosilicate, Boron Nitride, Polyglyceryl-10 Pentaisostearate, Lauroyl Lysine, Triethoxycaprylylsilane, Ethylhexylglycerin, Water (Aqua), Nylon-12, Propanediol, Sodium Dehydroacetate, Oryza Sativa (Rice) Bran Extract, Aletris Farinosa Root Extract, Ascorbyl Palmitate, Helianthus Annuus (Sunflower) Seed Extract, Tocopherol, Rosmarinus Officinalis (Rosemary) Leaf Extract, Titanium Dioxide (Cl 77891), Iron Oxides (Cl 77492, 77491, 77499)

PACKAGE LABEL

(Glow)Setting 100% Mineral Powder

SPF 35

Broad Spectrum Sunscreen

0.13 oz. / 3.7 g.